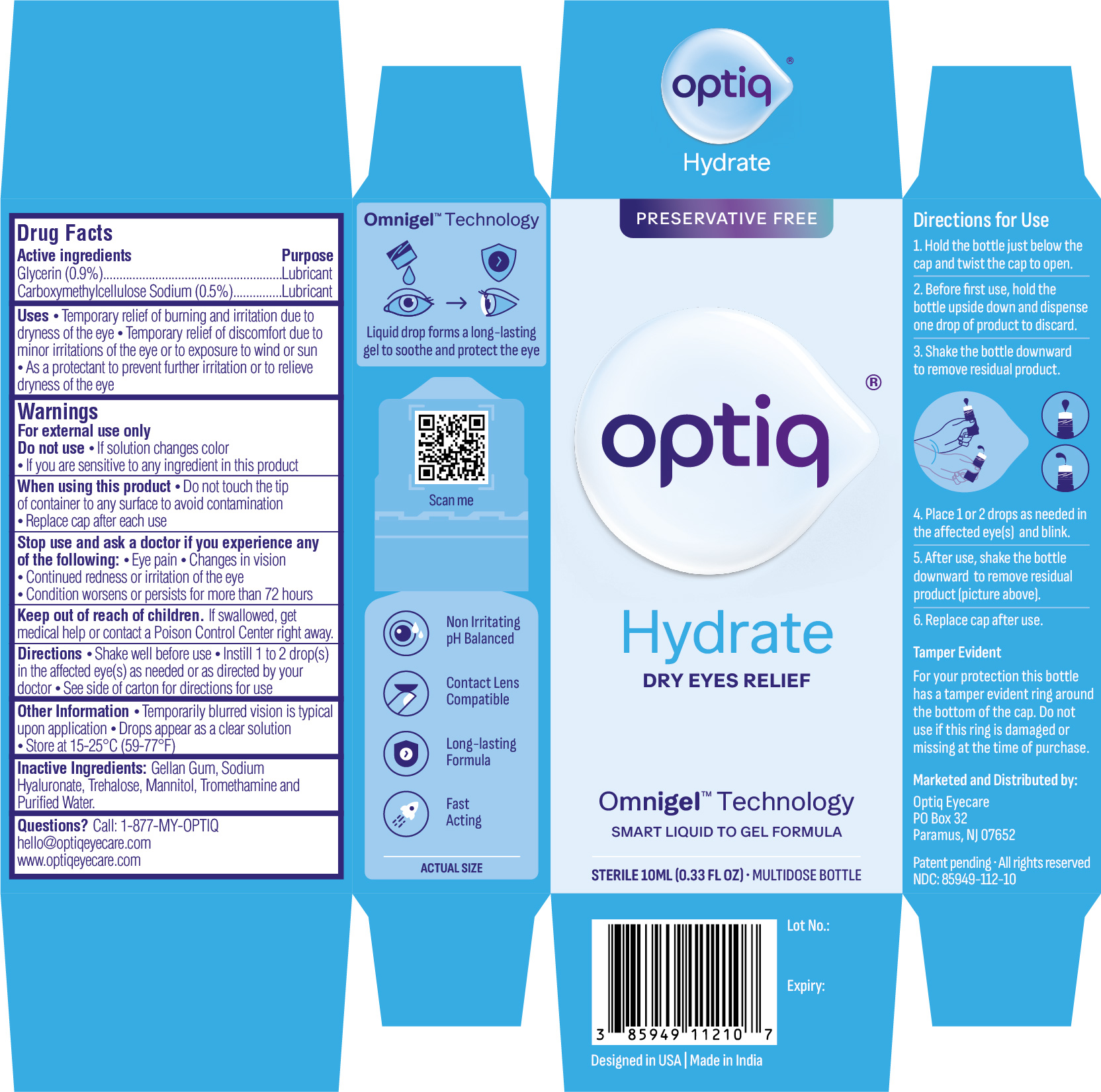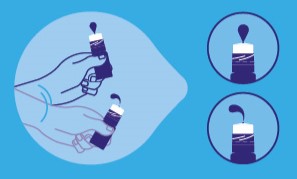 DRUG LABEL: Optiq Hydrate
NDC: 85949-112 | Form: SOLUTION
Manufacturer: Optiq Eyecare LLC
Category: otc | Type: HUMAN OTC DRUG LABEL
Date: 20250928

ACTIVE INGREDIENTS: GLYCERIN 9 mg/1 mL; CARBOXYMETHYLCELLULOSE SODIUM 5 mg/1 mL
INACTIVE INGREDIENTS: GELLAN GUM; SODIUM HYALURONATE; TREHALOSE DIHYDRATE; MANNITOL; TROMETHAMINE; WATER

OPTIQ
HYDRATE
DRY EYES RELIEF
PRESERVATIVE FREE

Drug Facts

Active Ingredients | Purpose
Glycerin (0.9%) | Lubricant
Ceryboxymethylcellulose Sodium (0.5%) | Lubricant

Uses

- Temporary relief of burning and irritation due to dryness of the eye
- Temporary relief of discomfort due to minor irritations of the eye or to exposure to wind or sun
- As a protectant to prevent further irritation or to relieve dryness of the eye

Warnings

For external use only

Do not use

- if solution changes color
- if you are sensitive to any ingredient in this product

When using this product

- Do not touch the tip of container to any surface to avoid contamination
- Replace cap after each use

Stop use and ask a doctor ifyou experience any of the following:

- Eye pain
- Changes in vision
- Continued redness or irritation of the eye
- Condition worsens or persists for more than 72 hours

Keep out of reach of children. If swallowed, get medical help or contact a Poison Control Center right away.

Directions

- Shake well before use
- Instill 1 to 2 drop(s) in the affected eye(s) as needed or as directed by your doctor
- See side of carton for directions for use

Other Information

- Temporarily blurred vision is typical upon application
- Drops appear as a clear solution
- Store at 15-25°C (59-77°F)

Inactive Ingredients

Gellan Gum, Sodium Hyaluronate, Trehalose, Mannitol, Tromethamine and Purified Water.

Questions?

Call: 1-877-696-7848

hello@optiqeyecare.com
www.optiqeyecare.com

Directions for Use:

1. Hold the bottle just below the cap and twist the cap to open.
2. Before first use, hold the bottle upside down and dispense one drop of product to discard.
3. Shake the bottle downward to remove residual product (see picture).

4. Place 1 or 2 drops as needed in the affected eye(s) and blink.
5. After use, shake the bottle downward to remove residual product that may be left on the tip (picture above).
6. Replace cap after use.

Tamper Evident

For your protection this bottle has a tamper evident ring around the bottom of the cap. Do not use if this ring is damaged or missing at the time of purchase.

Marketed and Distributed by:
Optiq Eyecare
PO Box 32
Paramus, NJ 07652

PRINCIPAL DISPLAY PANEL

Optiq Eyecare

NDC: 85949-112-10

Optiq

Hydrate

DRY EYES RELIEF